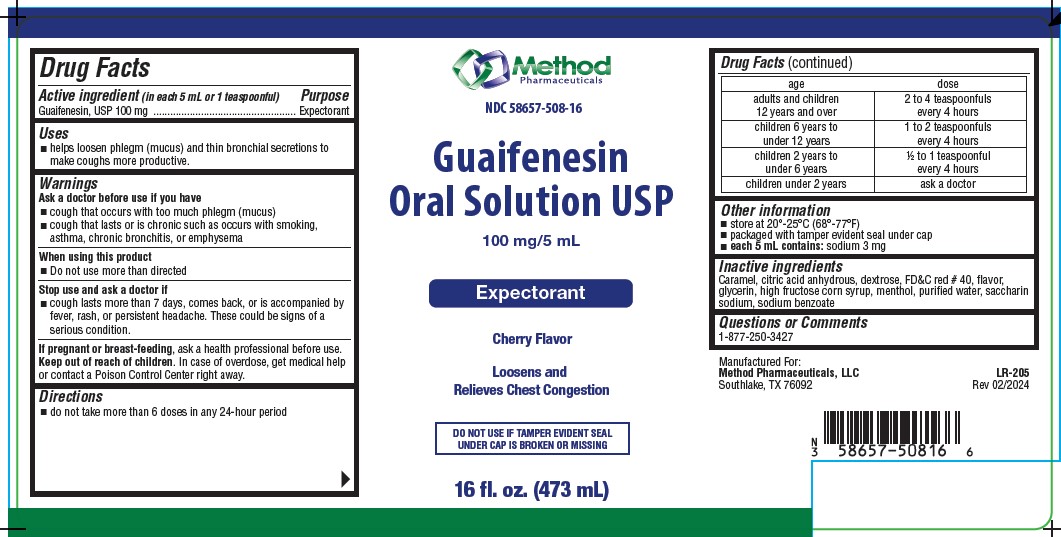 DRUG LABEL: Guaifenesin
NDC: 58657-508 | Form: LIQUID
Manufacturer: Method Pharmaceuticals, LLC
Category: otc | Type: HUMAN OTC DRUG LABEL
Date: 20251021

ACTIVE INGREDIENTS: GUAIFENESIN 100 mg/5 mL
INACTIVE INGREDIENTS: MENTHOL; CARAMEL; DEXTROSE; ANHYDROUS CITRIC ACID; FD&C RED NO. 40; GLYCERIN; WATER; SODIUM BENZOATE; SACCHARIN SODIUM; HIGH FRUCTOSE CORN SYRUP

Guaifenesin

NDC 58657-508-16

Guaifenesin

Liquid USP

100 mg/5 Ml

Expectorant

Sugar Free • Alcohol Free

Cherry Flavor

Loosens and Relieves Chest Congestion

16 fl. oz. (473 mL)

Drug Facts

Active ingredient (in each 5 mL)

Guaifenesin 100 mg

Purpose

Expectorant

Uses

- helps loosen phlegm (mucus) and thin bronchial secretions to make coughs more productive.

Warnings

Ask a doctor before use if you have

- cough that occurs with too much phlegm (mucus)
- cough that lasts or is chronic such as occurs with smoking, asthma, chronic bronchitis, or emphysema

When using this product

- Do not use more than directed

Stop use and ask a doctor if

- cough lasts more than 7 days, comes back, or is accompanied by fever, rash, or persistent headache. These could be signs of a serious condition.

If pregnant or breast-feeding,

ask a health professional before use.

Keep out of reach of children.

In case of overdose, get medical help or contact a Poison Control Center right away.

Directions

- do not take more than 6 doses in any 24-hour period
  age | dose
  adults and children 12 years and over | 2 to 4 teaspoonfuls every 4 hours
  children 6 years to under 12 years | 1 to 2 teaspoonfuls every 4 hours
  children 2 to under 6 yars | 1/2 to 1 teaspoonful every 4 hours
  children under 2 years | ask a doctor

Other information

- store at 20°-25°C (68°-77°F)
- packaged with tamper evident seal under cap
- each 5 mL contains: sodium 3 mg

Inactive ingredients

Caramel, citric acid anhydrous, dextrose, FD&C red #40, flavor, gylcerin, high fructose corn syrup, menthol, purified water, saccharin, sodium, sodium benzoate

Questions or Comments

1-877-250-3427

Manufactured For:
Method Pharmaceuticals, LLC
Southlake, TX 79092

LR-205

Rev-2024

PRINCIPAL DISPLAY PANEL

NDC 58657- 508- 16
Guaifenesin
Liquid USP
100 mg/ 5 mL
Expectorant
16 fl. oz. (473 mL)